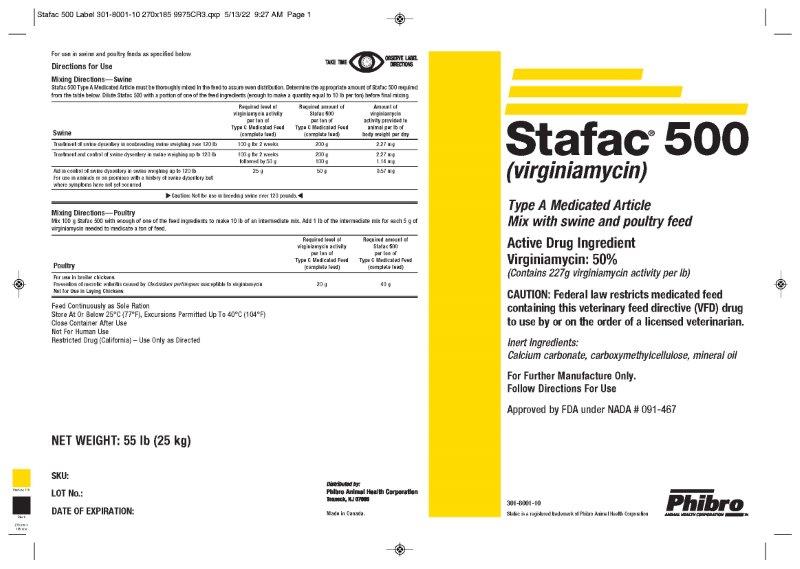 DRUG LABEL: Stafac 500
NDC: 66104-1501 | Form: POWDER
Manufacturer: Phibro Animal Health
Category: animal | Type: VFD TYPE A MEDICATED ARTICLE ANIMAL DRUG LABEL
Date: 20231106

ACTIVE INGREDIENTS: VIRGINIAMYCIN 227 g/0.45 kg
INACTIVE INGREDIENTS: CALCIUM CARBONATE; MINERAL OIL; CARBOXYMETHYLCELLULOSE SODIUM, UNSPECIFIED FORM; SOYBEAN OIL

Stafac® 500
(Virginiamycin)
TYPE A MEDICATED ARTICLE

Type A Medicated Article Mix with swine and poultry feed

Active Drug Ingredient

Virginiamycin : 50%

(Contains 227g virginiamycin activity per lb)

Caution

CAUTION: Federal law restricts medicated feed containing this veterinary feed directive (VFD) drug to use by or on the order of a licensed veterinarian.

Inert Ingredients:

Calcium carbonate, carboxymethylcellulose, mineral oil

For Further Manufacture Only.

Follow Directions For Use.

Approved by FDA under NADA # 091-467

301-8001-10

Stafac is a registered trademark of Phibro Animal Health Corporation

Distributed by: Phibro Animal Health Corporation, Teaneck, NJ 07666

Made in Canada

Directions for Use

Mixing Directions—Swine

Stafac 500 Type A Medicated Article must be thoroughly mixed in the feed to assure even distribution. Determine the appropriate amount of Stafac 500 required from the table below. Dilute Stafac 500 with a portion of one of the feed ingredients (enough to make a quantity equal to 10 lb per ton) before final mixing.

Swine | Required level of virginiamycin activity per ton of Type C Medicated Feed (complete feed) | Required amount of Stafac 500 per ton of Type C Medicated Feed (complete feed) | Amount of virginiamycin activity provided to animal per lb of body weight per day
Treatment of swine dysentery in nonbreeding swine weighing over 120 lb | 100 g for 2 weeks | 200 g | 2.27 mg
Treatment and control of swine dysentery in swine weighing up to 120 lb | 100 g for 2 weeks; followed by 50 g | 200 g; 100 g | 2.27 mg; 1.14 mg
Aid in control of swine dysentery in swine weighing up to 120 lb; For use in animals or on premises with a history of swine dysentery but where symptoms have not yet occurred | 25 g | 50 g | 0.57 mg
►Caution: Not for use in breeding swine over 120 pounds.◄
Mixing Directions—Poultry
Mix 100 g Stafac 500 with enough of one of the feed ingredients to make 10 lb of an intermediate mix. Add 1 lb of the intermediate mix for each 5 g of virginiamycin needed to medicate a ton of feed.
Poultry |  | Required level of virginiamycin activity per ton of Type C Medicated Feed (complete feed) | Required amount of Stafac 500 per ton of Type C Medicated Feed (complete feed)
For use in broiler chickens
Prevention of necrotic enteritis caused by Clostridium perfringens susceptible to virginiamycin |  | 20 g | 40 g
Not for Use in Laying Chickens

Storage and Handling

Feed Continuously as Sole Ration

Store At Or Below 25oC (77oF), Excursions Permitted Up to 40oC (104oF)

Close Container After Use

NOT FOR HUMAN USE

Restricted Drug (California) – Use Only as Directed

Stafac 500